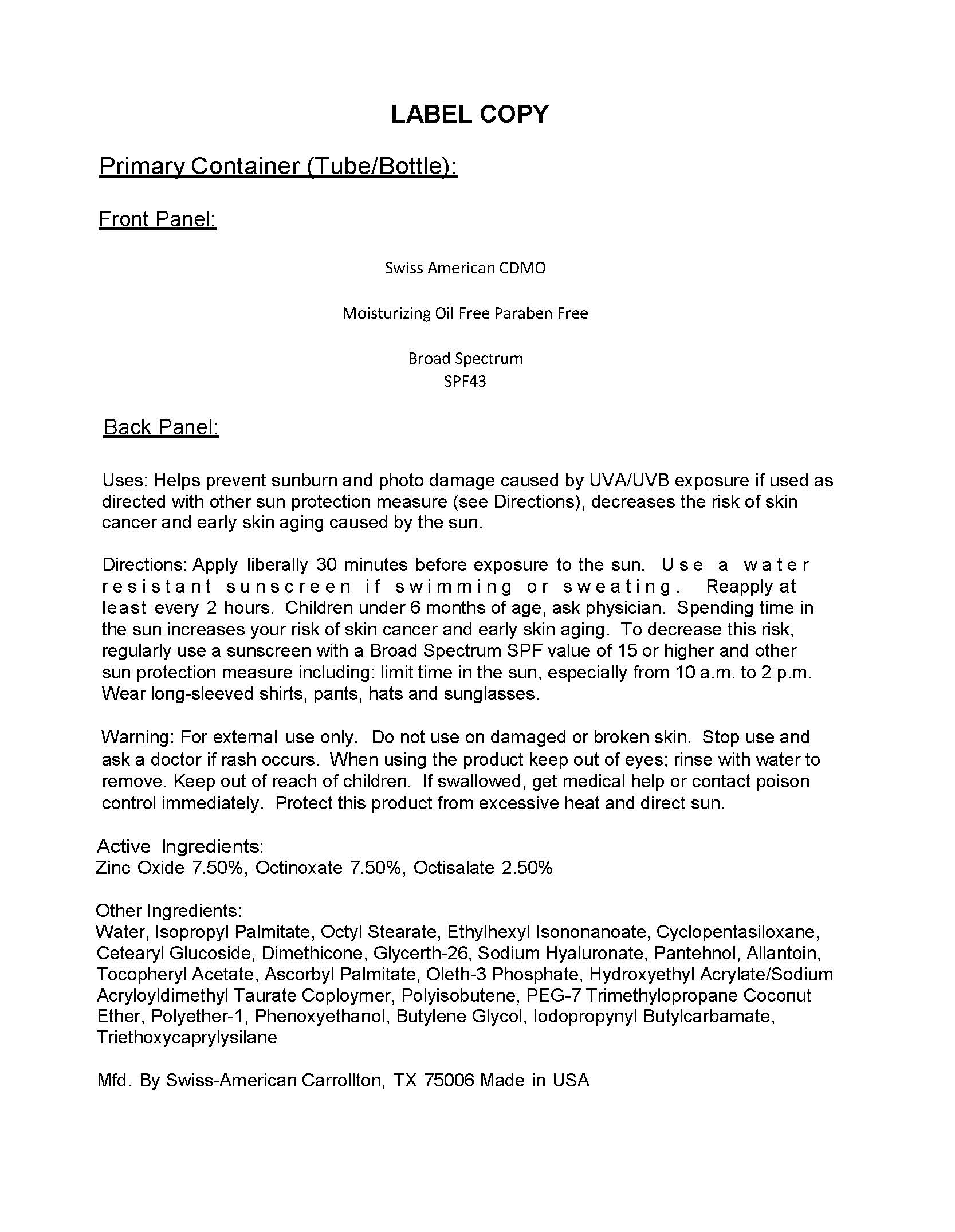 DRUG LABEL: Private Label Moisturizing Oil Free Paraben Free SPF43
NDC: 60232-0007 | Form: LOTION
Manufacturer: Swiss-American CDMO, LLC
Category: otc | Type: HUMAN OTC DRUG LABEL
Date: 20231107

ACTIVE INGREDIENTS: ZINC OXIDE 75 g/1000 g; OCTINOXATE 75 g/1000 g; OCTISALATE 25 g/1000 g
INACTIVE INGREDIENTS: WATER; GLYCERETH-26; PHENOXYETHANOL; DIMETHICONE; ISOPROPYL PALMITATE; OCTYL STEARATE; OLETH-3 PHOSPHATE; ETHYLHEXYL ISONONANOATE; PANTHENOL; ALLANTOIN; HYALURONIC ACID; CYCLOMETHICONE 5; .ALPHA.-TOCOPHEROL ACETATE; BUTYLENE GLYCOL; IODOPROPYNYL BUTYLCARBAMATE; HYDROXYETHYL ACRYLATE/SODIUM ACRYLOYLDIMETHYL TAURATE COPOLYMER (45000 MPA.S AT 1%); TRIETHOXYCAPRYLYLSILANE

Private Label Moisturizing Oil Free Paraben Free SPF43

Warnings

For external use only. Do not use on damaged or broken skin. Stope use and ask doctor if rash occurs. When using the product keep out of eyes; rinse with water to remove. Keep out of reach of children. If swallowed, get medical help or contact poison control immediately. Protect this product from excessive heat and direct sun.

Uses

Helps prevent sunbrun an dphoto damage caused by UVA/UVB exposure. If used as directed with other sun protection measures (see directions) , decreases the risk of skin cancer and early skin aging caused by the sun.

Uses

Helps prevent sunbrun an dphoto damage caused by UVA/UVB exposure. If used as directed with other sun protection measures (see directions) , decreases the risk of skin cancer and early skin aging caused by the sun.

Directions

Apply liberally 15 minutes before exposure to the sun. Use a water resistant sunscreen if swimming or sweating. Reapply at least every 2 hours. Children under 6 months of age, ask physician. Spending time in the sun increases your risk of skin cancer and early skin aging. To decrease this risk, regularly use a sunscreen with a broad spectrum SPF value of 15 or higher and other sun protection measures including: limit time in the sun, especially from 10 a.m. to 2 p.m. Wear long-sleeved shirts, pants, hats and sunglasses.

Active Ingredients

Zinc Oxide 7.50%

Octinoxate 7.50%

Octisalate 2.50%

Keep out of reach of children

Other Ingredients

Water, Isopropyl Palmitate, Octyl Stearate, Ethylhexyl Isononanoate, Cylcopentasiloxane, Cetearyl Glucoside, Dimethicone, Glycerth-26, Sodium Hyaluronate, Panthenol, Allantoin, Tocopheryl Acetate, Ascorbyl Palmitate, Oleth-3 Phosphate, Hydroxyethyl Acrylate/Sodium Acryloyldimethyl Taurate Copolymer, Polyisobutene, PEG-7 Trimethylopropane Coconut Ether, Polyether-1, Phenoxyethanol, Butylene Glycol, Iodopropynyl Butylcarbamate, Triethoxycaprylysilane